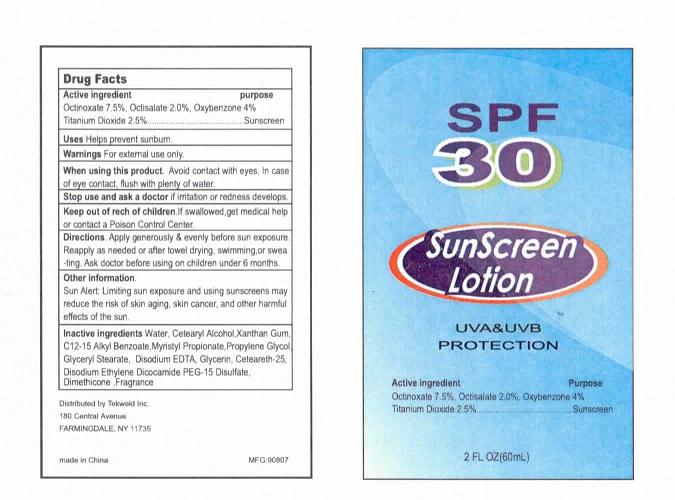 DRUG LABEL: SunScreen SPF30
NDC: 31190-500 | Form: LOTION
Manufacturer: Shanghai Kejing Cleaning Products Co., Ltd.
Category: otc | Type: HUMAN OTC DRUG LABEL
Date: 20100614

ACTIVE INGREDIENTS: OCTINOXATE 7.5 mL/100 mL; OCTISALATE 2 mL/100 mL; OXYBENZONE 4 mL/100 mL; TITANIUM DIOXIDE 2.5 mL/100 mL
INACTIVE INGREDIENTS: WATER; CETOSTEARYL ALCOHOL; XANTHAN GUM; C12-15 ALKYL BENZOATE; PROPYLENE GLYCOL; GLYCERYL MONOSTEARATE; EDETATE DISODIUM; GLYCERIN; DIMETHICONE

SunScreen Lotion SPF30

Active ingredient Purpose

Octinoxate 7.8 percent, Octisalate 2.0 percent, Oxybenzone 4 percent

Titanium Dioxide 2.5 percent........................................................................ Sunscreen

PURPOSE

Uses: Helps prevent sunburn

Warnings: For external use only.

When using this product: Avoid contact with eyes, In case of eye contact, flush with plenty of water.

Stop use and ask a doctor if irritation or redness develops.

Keep out of reach of children. If swallowed, get medical help
or contact a Poison Control Center.

DOSAGE AND ADMINISTRATION

Directions. Apply generously and evenly before sun exposure.
Reapply as needed or after towel drying, swimming,or sweating. Ask doctor before using on children under 6 months.

Other information.
Sun Alert: Limiting sun exposure and using sunscreens may
reduce the risk of skin aging, skin cancer, and other harmful
effects of the sun.

SPF30 SUNSCREEN SPRAY

UVAand UVB PROTECTION

Distributed by Tekweld Inc.
180 Central Avenue,
FARMINGDALE,NY11735

made in China MFG:90807

INACTIVE INGREDIENT

Inactive Ingredients Water, Cetearyl Alcohol, Xanthan Gum, C12-15 Alkyl Benzoate, Myristyl Propionate, Propylene Glycol, Glyceryl Stearate, Disodium EDTA, Glycerin, Ceteareth-25,

Disodium Ethylene Dicocamide PEG-15 Disulfate, Dimethicone, Fragrance